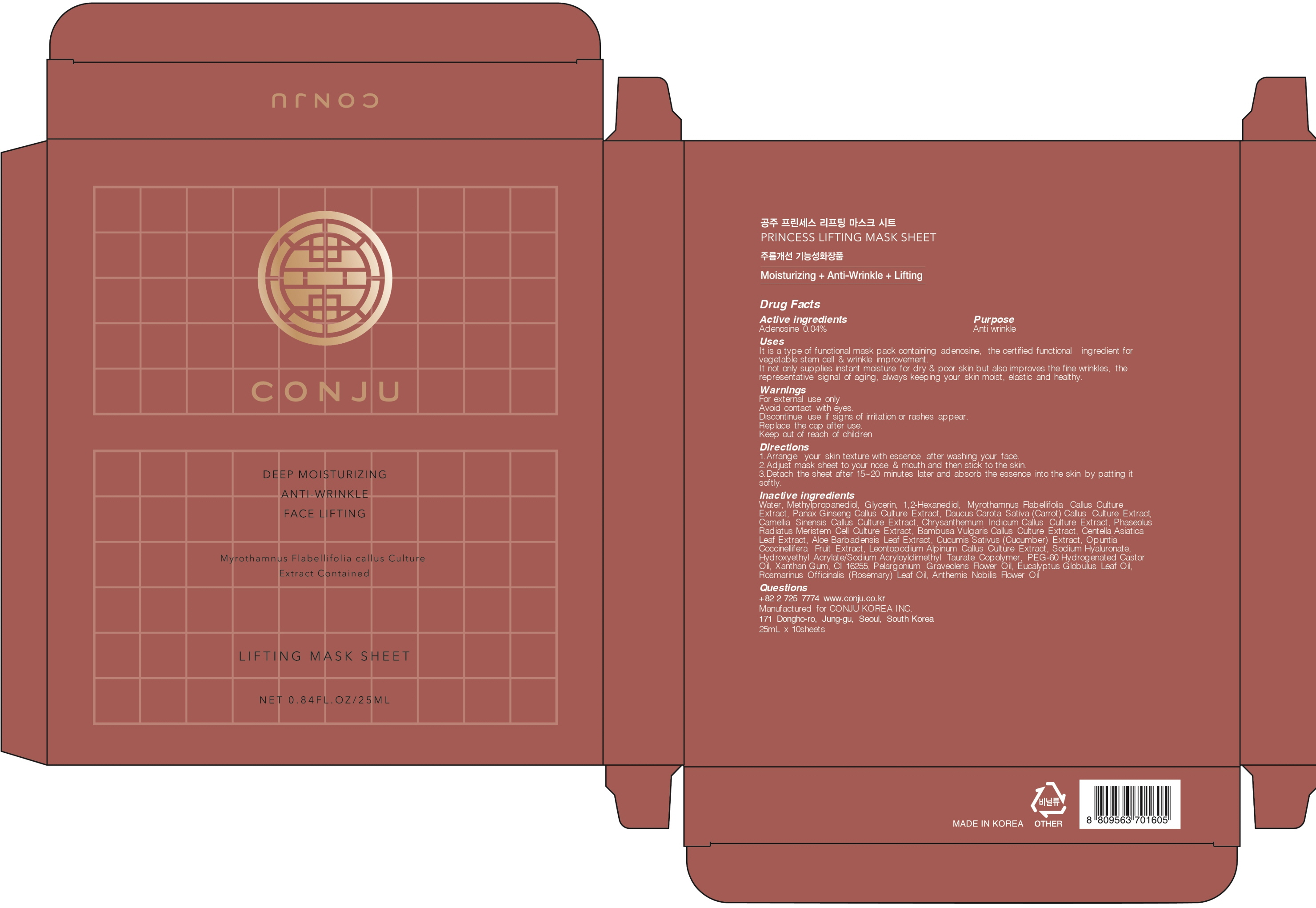 DRUG LABEL: CONGJU PRINCESS LIFTING MASK SHEET
NDC: 72950-040 | Form: PATCH
Manufacturer: Conju Korea Inc.
Category: otc | Type: HUMAN OTC DRUG LABEL
Date: 20190318

ACTIVE INGREDIENTS: Adenosine 0.01 g/25 mL
INACTIVE INGREDIENTS: Water; Methylpropanediol

ACTIVE INGREDIENT

Active ingredients: Adenosine 0.04%

INACTIVE INGREDIENT

Inactive ingredients:
Water, Methylpropanediol, Glycerin, 1,2-Hexanediol, Myrothamnus Flabellifolia Callus Culture Extract, Panax Ginseng Callus Culture Extract, Daucus Carota Sativa (Carrot) Callus Culture Extract, Camellia Sinensis Callus Culture Extract, Chrysanthemum Indicum Callus Culture Extract, Phaseolus Radiatus Meristem Cell Culture Extract, Bambusa Vulgaris Callus Culture Extract, Centella Asiatica Leaf Extract, Aloe Barbadensis Leaf Extract, Cucumis Sativus (Cucumber) Extract, Opuntia Coccinellifera Fruit Extract, Leontopodium Alpinum Callus Culture Extract, Sodium Hyaluronate, Hydroxyethyl Acrylate/Sodium Acryloyldimethyl Taurate Copolymer, PEG-60 Hydrogenated Castor Oil, Xanthan Gum, CI 16255, Pelargonium Graveolens Flower Oil, Eucalyptus Globulus Leaf Oil, Rosmarinus Officinalis (Rosemary) Leaf Oil, Anthemis Nobilis Flower Oil

PURPOSE

Purpose: Anti wrinkle

WARNINGS

For external use only
Avoid contact with eyes.
Discontinue use if signs of irritation or rashes appear.
Replace the cap after use.
Keep out of reach of children

KEEP OUT OF REACH OF CHILDREN

Uses

It is a type of functional mask pack containing adenosine, the certified functional ingredient for vegetable stem cell & wrinkle improvement.
It not only supplies instant moisture for dry & poor skin but also improves the fine wrinkles, the representative signal of aging, always keeping your skin moist, elastic and healthy.

Directions

1. Arrange your skin texture with essence after washing your face.
2. Adjust mask sheet to your nose & mouth and then stick to the skin.
3. Detach the sheet after 15~20 minutes later and absorb the essence into the skin by patting it softly.